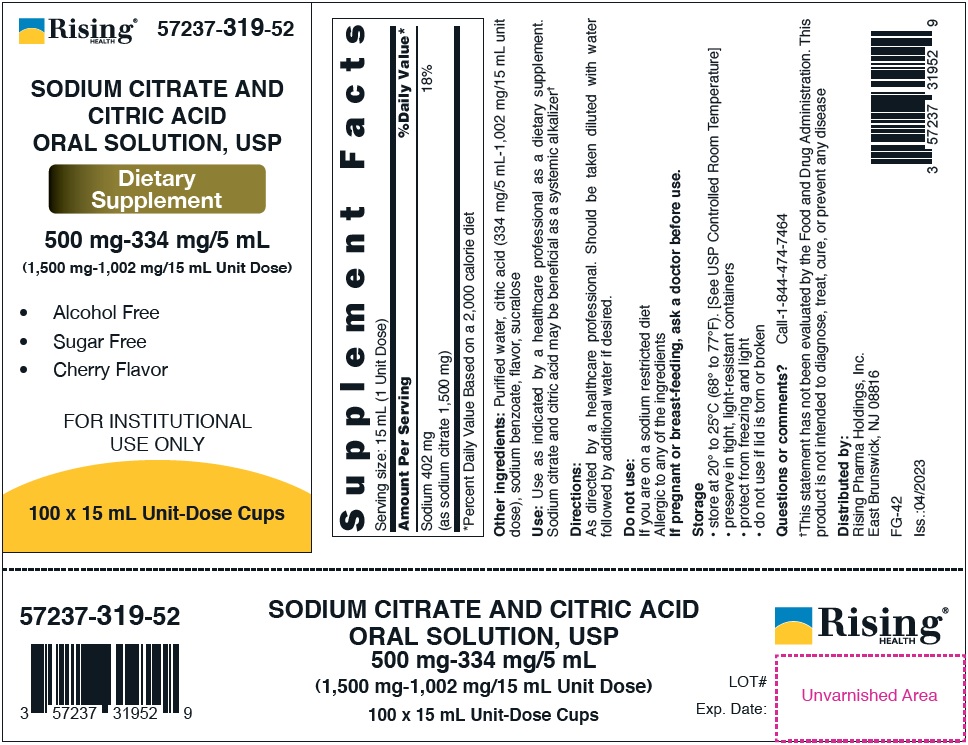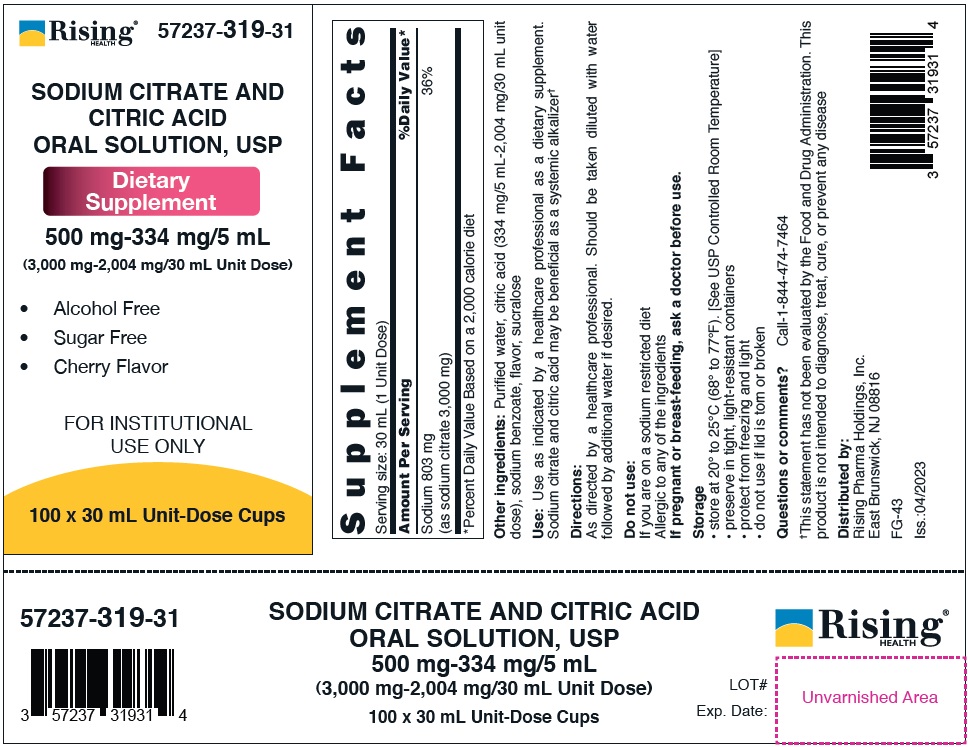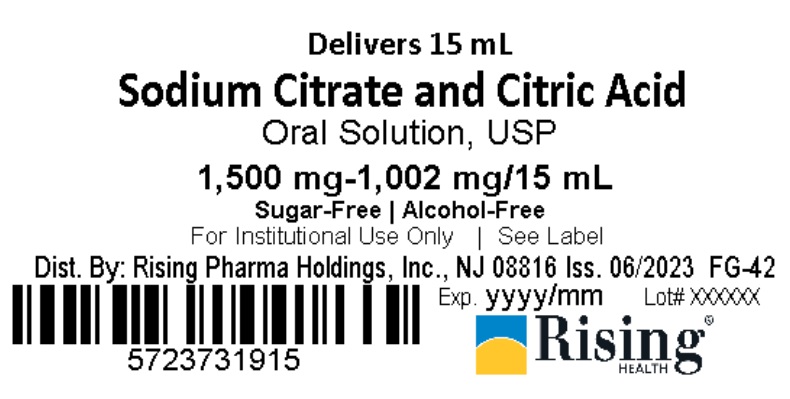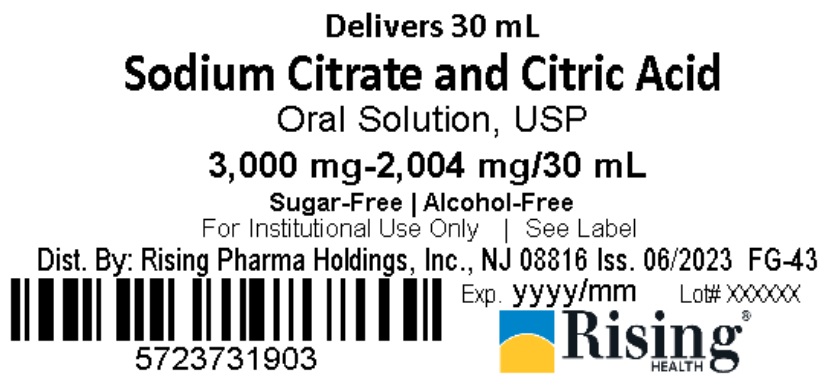 DRUG LABEL: SODIUM CITRATE AND CITRIC ACID
NDC: 57237-319 | Form: SOLUTION
Manufacturer: Rising Pharma Holdings, Inc.
Category: other | Type: DIETARY SUPPLEMENT
Date: 20250515

ACTIVE INGREDIENTS: SODIUM CITRATE, UNSPECIFIED FORM 500 mg/5 mL; ANHYDROUS CITRIC ACID 334 mg/5 mL
INACTIVE INGREDIENTS: CITRIC ACID; SODIUM BENZOATE; SUCRALOSE; WATER

SODIUM CITRATE AND CITRIC ACID ORAL SOLUTION, USP
500 mg-334 mg/5 mL (1,500 mg-1,002 mg/15 mL Unit Dose)
500 mg-334 mg/5 mL (3,000 mg-2,004 mg/30 mL Unit Dose)
Dietary Supplement - FOR INSTITUTIONAL USE ONLY
• Alcohol Free
• Sugar Free
• Cherry Flavor

STATEMENT OF IDENTITY

Supplement Facts

Serving Size: 15 mL (1 Unit Dose)

Amount Per Serving

% Daily Value*

Sodium 402 mg

18%

(as sodium citrate 1,500 mg)

*Percent Daily Value Based on a 2,000 calorie diet

Supplement Facts

Serving size: 30 mL (1 Unit Dose)

Amount Per Serving

%Daily Value*

Sodium 803 mg

36%

(as sodium citrate 3,000 mg)

*Percent Daily Value Based on a 2,000 calorie diet

HEALTH CLAIM

Other ingredients: For 1,500 mg-1,002 mg/15 mL Unit Dose - Purified water, citric acid (334 mg/5 mL-1,002 mg/15 mL unit dose), sodium benzoate, flavor, sucralose

For 3,000 mg-2,004 mg/30 mL Unit Dose - Purified water, citric acid (334 mg/5 mL-2,004 mg/30 mL unit dose), sodium benzoate, flavor, sucralose

Use: Use as indicated by a healthcare professional as a dietary supplement. Sodium citrate and citric acid may be beneficial as a systemic alkalizer†

Directions:

As directed by a healthcare professional. Should be taken diluted with water followed by additional water if desired.

Do not use:

If you are on a sodium restricted diet

Allergic to any of the ingredients

PRECAUTIONS

If pregnant or breast-feeding, ask a doctor before use.

DOSAGE AND ADMINISTRATION

Storage
• store at 20° to 25°C (68° to 77°F). [See USP Controlled Room Temperature]
• preserve in tight, light-resistant containers
• protect from freezing and light
• do not use if lid is torn or broken

Questions or comments? Call-1-844-474-7464
†This statement has not been evaluated by the Food and Drug Administration. This product is not intended to diagnose, treat, cure, or prevent any disease

Distributed by:
Rising Pharma Holdings, Inc.
East Brunswick, NJ 08816
FG-42 (for 15 mL)

FG-43 (for 30 mL)
Iss.:04/2023

PACKAGE LABEL

500 mg-334 mg/5 mL (1,500 mg-1,002 mg/15 mL Unit Dose)

Case label -

57237-319-52 (100 x 15 mL Unit-Dose Cups)

Lid Label -

57237-319-15 (Delivers 15 mL)

500 mg-334 mg/5 mL (3,000 mg-2,004 mg/30 mL Unit Dose)

Case label -

57237-319-31 (100 x 30 mL Unit-Dose Cups)

Lid Label -

57237-319-03 (Delivers 30 mL)